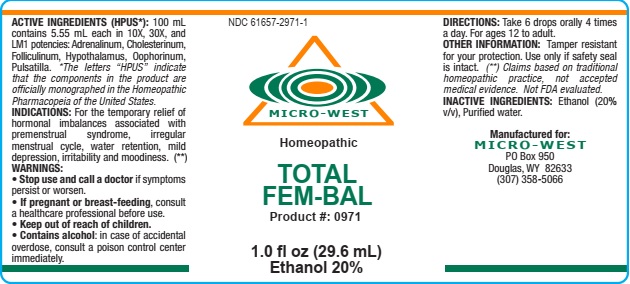 DRUG LABEL: TOTAL FEM BAL
NDC: 61657-2971 | Form: LIQUID
Manufacturer: White Manufacturing Inc. DBA Micro-West
Category: homeopathic | Type: HUMAN PRESCRIPTION DRUG LABEL
Date: 20210121

ACTIVE INGREDIENTS: EPINEPHRINE 10 [hp_X]/30 mL; CHOLESTEROL 10 [hp_X]/30 mL; ESTRONE 10 [hp_X]/30 mL; BOS TAURUS HYPOTHALAMUS 10 [hp_X]/30 mL; SUS SCROFA OVARY 10 [hp_X]/30 mL; ANEMONE PULSATILLA 10 [hp_X]/30 mL
INACTIVE INGREDIENTS: ALCOHOL; WATER

TOTAL FEM BAL

ACTIVE INGREDIENTS (HPUS*): 100 mL
contains 5.55 mL each in 10X, 30X, and
LM1 potencies: Adrenalinum, Cholesterinum,
Folliculinum, Hypothalamus, Oophorinum,
Pulsatilla. *The letters “HPUS” indicate
that the components in the product are
officially monographed in the Homeopathic
Pharmacopeia of the United States.

INDICATIONS: For the temporary relief of
hormonal imbalances associated with
premenstrual syndrome, irregular
menstrual cycle, water retention, mild
depression, irritability and moodiness. (**)

WARNINGS:
• Stop use and call a doctor if symptoms
persist or worsen.
• If pregnant or breast-feeding, consult
a healthcare professional before use.
• Keep out of reach of children.
• Contains alcohol: in case of accidental
overdose, consult a poison control center
immediately.

DOSAGE AND ADMINISTRATION

DIRECTIONS: Take 6 drops orally 4 times
a day. For ages 12 to adult.

OTHER INFORMATION: Tamper resistant
for your protection. Use only if safety seal
is intact. (**) Claims based on traditional
homeopathic practice, not accepted
medical evidence. Not FDA evaluated

INACTIVE INGREDIENTS: Ethanol (20%
v/v), Purified water.

PACKAGE LABEL

NDC 61657-2971-1

MICRO-WEST

Homeopathic

TOTAL

FEM-BAL

Product #: 0971

1.0 fl oz (29.6 mL)

Ethanol 20%

PURPOSE

For the temporary relief of
hormonal imbalances associated with
premenstrual syndrome, irregular
menstrual cycle, water retention, mild
depression, irritability and moodiness. (**)